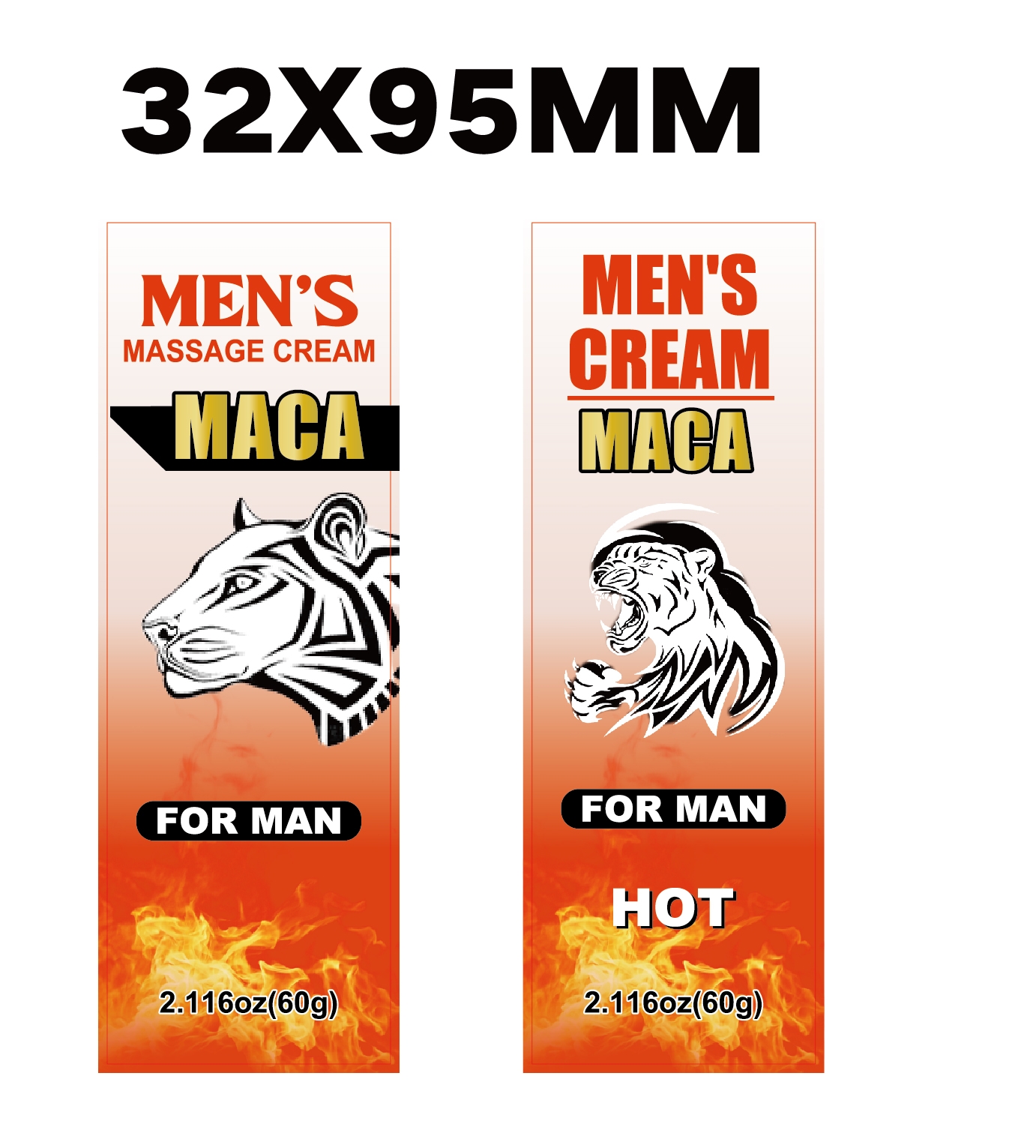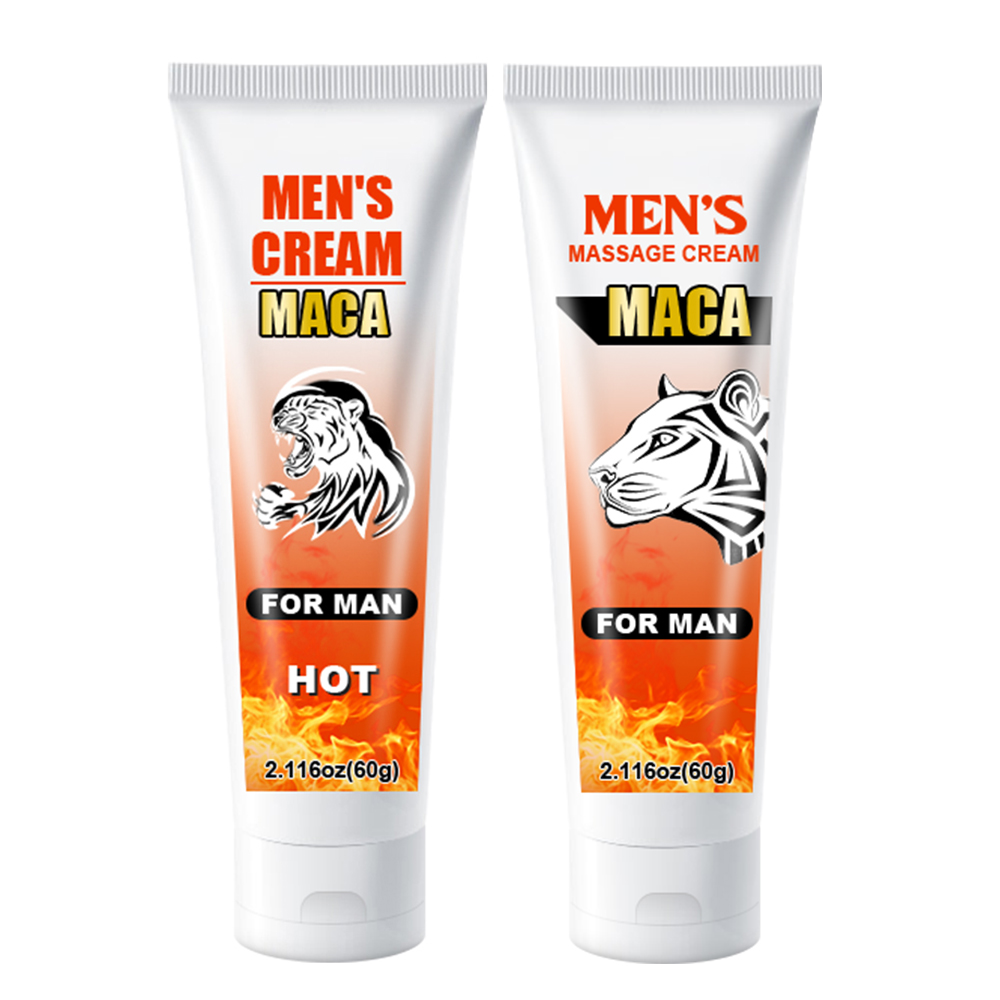 DRUG LABEL: Mens Massage Cream
NDC: 84025-300 | Form: CREAM
Manufacturer: Guangzhou Yanxi Biotechnology Co., Ltd
Category: otc | Type: HUMAN OTC DRUG LABEL
Date: 20241230

ACTIVE INGREDIENTS: GLYCERIN 5 mg/100 g; PANTHENOL 3 mg/100 g
INACTIVE INGREDIENTS: WATER

DOSAGE AND ADMINISTRATION

So easy to use, simply apply the appropriate amount of breast enhancement to a clean, private area and gently massage into full absorption

WARNINGS

keep out of chlidren

INACTIVE INGREDIENT

Aqua

INDICATIONS AND USAGE

Men's Massage Cream can help restore your drive and get you feeling more like the man you are.

keep out of children

PURPOSE

MOISTURIZING SKlIN:Skin absorbs it easily, leaving skinhydrated, smooth, Deep moisturizing and nourishing skin, nongreasy, no sticky residue